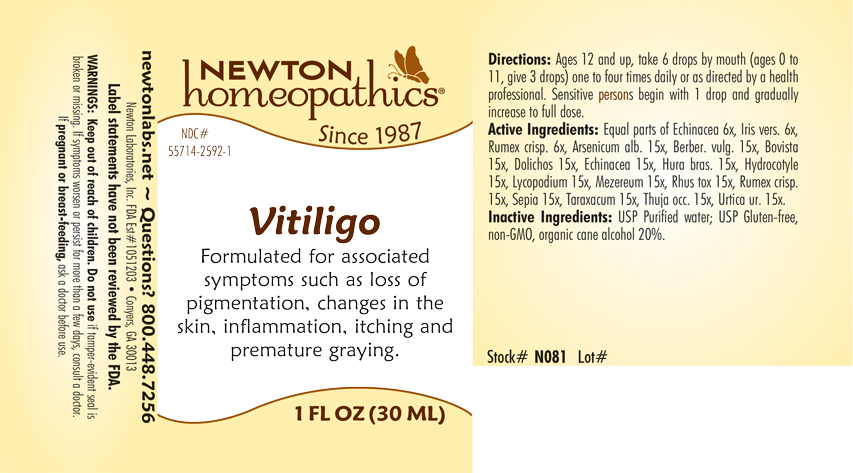 DRUG LABEL: Vitiligo
NDC: 55714-2592 | Form: LIQUID
Manufacturer: Newton Laboratories, Inc.
Category: homeopathic | Type: HUMAN OTC DRUG LABEL
Date: 20240311

ACTIVE INGREDIENTS: ECHINACEA, UNSPECIFIED 15 [hp_X]/1 mL; HURA CREPITANS SAP 15 [hp_X]/1 mL; CENTELLA ASIATICA 15 [hp_X]/1 mL; LYCOPODIUM CLAVATUM SPORE 15 [hp_X]/1 mL; DAPHNE MEZEREUM BARK 15 [hp_X]/1 mL; TOXICODENDRON PUBESCENS LEAF 15 [hp_X]/1 mL; RUMEX CRISPUS ROOT 15 [hp_X]/1 mL; SEPIA OFFICINALIS JUICE 15 [hp_X]/1 mL; TARAXACUM OFFICINALE 15 [hp_X]/1 mL; THUJA OCCIDENTALIS LEAFY TWIG 15 [hp_X]/1 mL; URTICA URENS 15 [hp_X]/1 mL; ARSENIC TRIOXIDE 15 [hp_X]/1 mL; BERBERIS VULGARIS ROOT BARK 15 [hp_X]/1 mL; IRIS VERSICOLOR ROOT 6 [hp_X]/1 mL; LYCOPERDON UTRIFORME FRUITING BODY 15 [hp_X]/1 mL; MUCUNA PRURIENS FRUIT TRICHOME 15 [hp_X]/1 mL
INACTIVE INGREDIENTS: WATER; ALCOHOL

Vitiligo 2592L

INDICATIONS & USAGE SECTION

Formulated for associated symptoms such as loss of pigmentation, changes in the skin, inflammation, itching and premature graying.

DOSAGE & ADMINISTRATION SECTION

Directions: Ages 12 and up, take 6 drops by mouth (ages 0 to 11, give 3 drops) one to four times daily or as directed by a health professional. Sensitive persons begin with 1 drop and gradually increase to full dose.

OTC - ACTIVE INGREDIENT SECTION

Equal parts of Echinacea 6x, Iris versicolor 6x, Rumex crispus 6x, Arsenicum alb. 15x, Berber. vulg. 15x, Bovista 15x, Dolichos 15x, Echinacea 15x, Hura bras. 15x, Hydrocotyle 15x, Lycopodium 15x, Mezereum 15x, Rhus tox 15x, Rumex crisp. 15x, Sepia 15x, Taraxacum 15x, Thuja occ. 15x, Urtica ur. 15x.

OTC - PURPOSE SECTION

Formulated for associated symptoms such as loss of pigmentation, changes in the skin, inflammation, itching and premature graying.

INACTIVE INGREDIENT SECTION

Inactive Ingredients: USP Purified Water; USP Gluten-free, non-GMO, organic cane alcohol 20%.

QUESTIONS SECTION

newtonlabs.net – Questions? 800.448.7256

Newton Laboratories, Inc. FDA Est # 1051203 - Conyers, GA 30013

OTC - PREGNANCY OR BREAST FEEDING SECTION

If pregnant or breast-feeding, ask a doctor before use.

WARNINGS SECTION

WARNINGS: Keep out of reach of children. Do not use if tamper-evident seal is broken or missing. If symptoms worsen or persist for more than a few days, consult a doctor. If pregnant or breast-feeding, ask a doctor before use.

OTC - KEEP OUT OF REACH OF CHILDREN SECTION

Keep out of reach of children.